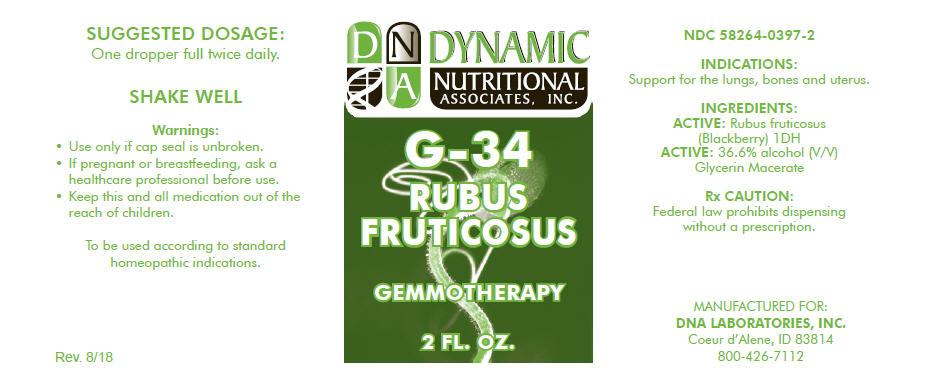 DRUG LABEL: G-34
NDC: 58264-0397 | Form: SOLUTION
Manufacturer: DNA Labs, Inc.
Category: homeopathic | Type: HUMAN OTC DRUG LABEL
Date: 20250109

ACTIVE INGREDIENTS: RUBUS FRUTICOSUS LEAF 1 [hp_X]/1 mL
INACTIVE INGREDIENTS: ALCOHOL; WATER

G-34

NDC 58264-0397-2

INDICATIONS

PURPOSE

Support for the lungs, bones and uterus.

INGREDIENTS

ACTIVE

Rubus fruticosus (Blackberry) 1DH

ACTIVE

36.6% alcohol (V/V) Glycerin Macerate

Rx CAUTION

Federal law prohibits dispensing without a prescription.

SUGGESTED DOSAGE

One dropper full twice daily.

STORAGE AND HANDLING

SHAKE WELL

Warnings

- Use only if cap seal is unbroken.

PREGNANCY OR BREAST FEEDING

- If pregnant or breastfeeding, ask a healthcare professional before use.

KEEP OUT OF REACH OF CHILDREN

- Keep this and all medication out of the reach of children.

To be used according to standard homeopathic indications.

PRINCIPAL DISPLAY PANEL - 2 FL. OZ. Bottle Label

DYNAMIC
NUTRITIONAL
ASSOCIATES, INC.

G-34

RUBUS
FRUTICOSUS

GEMMOTHERAPY

2 FL. OZ.